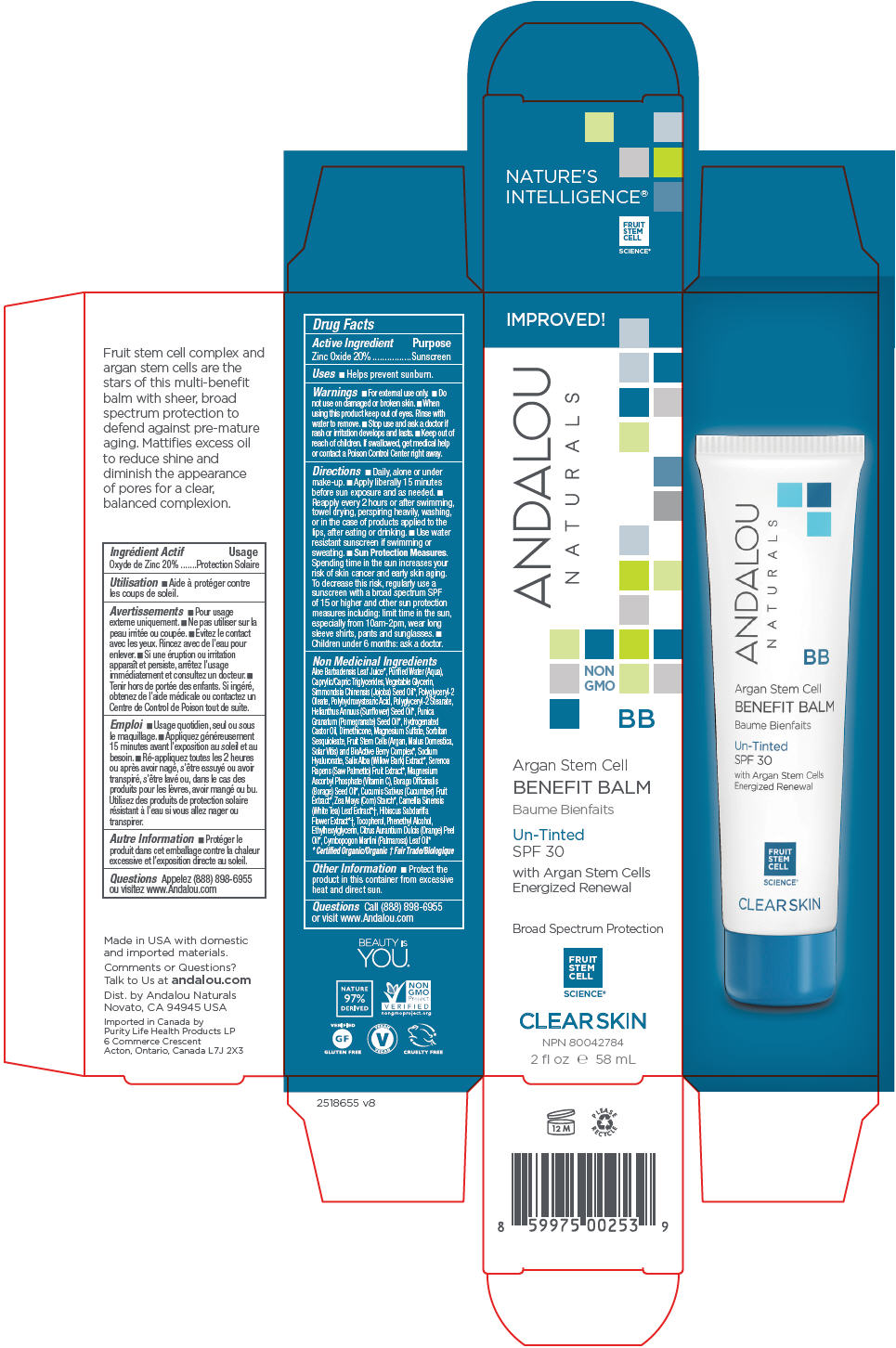 DRUG LABEL: Argan Stem Cell BB Benefit Balm Un-Tinted SFP 30
NDC: 55560-0109 | Form: LOTION
Manufacturer: Andalou naturals
Category: otc | Type: HUMAN OTC DRUG LABEL
Date: 20190724

ACTIVE INGREDIENTS: ZINC OXIDE 200 mg/1 mL
INACTIVE INGREDIENTS: ALOE VERA LEAF; WATER; MEDIUM-CHAIN TRIGLYCERIDES; GLYCERIN; JOJOBA OIL; POLYHYDROXYSTEARIC ACID (2300 MW); POLYGLYCERYL-2 STEARATE; SUNFLOWER OIL; POMEGRANATE SEED OIL; HYDROGENATED CASTOR OIL; DIMETHICONE; MAGNESIUM SULFATE, UNSPECIFIED FORM; SORBITAN SESQUIOLEATE; APPLE; VITIS VINIFERA SEED; ACAI; ARONIA MELANOCARPA FRUIT JUICE; ARCTOSTAPHYLOS UVA-URSI LEAF; VACCINIUM MYRTILLUS ANTHOCYANOSIDES; EUROPEAN ELDERBERRY JUICE; LYCIUM BARBARUM FRUIT; ROSA CANINA FRUIT; HIPPOPHAE RHAMNOIDES FRUIT; HYALURONATE SODIUM; WILLOW BARK; SAW PALMETTO; MAGNESIUM ASCORBYL PHOSPHATE; BORAGE SEED OIL; CUCUMBER; STARCH, CORN; WHITE TEA; HIBISCUS SABDARIFFA FLOWER; TOCOPHEROL; PHENYLETHYL ALCOHOL; ETHYLHEXYLGLYCERIN; ORANGE OIL, COLD PRESSED; PALMAROSA OIL

Argan Stem Cell BB Benefit Balm Un-Tinted SFP 30

Drug Facts

Active Ingredient

Zinc Oxide 20%

Purpose

Sunscreen

Uses

- Helps prevent sunburn.

Warnings

- For external use only.

- Do not use on damaged or broken skin.

- When using this product keep out of eyes. Rinse with water to remove.

- Stop use and ask a doctor if rash or irritation develops and lasts.

- Keep out of reach of children. If swallowed, get medical help or contact a Poison Control Center right away.

Directions

- Daily, alone or under make-up.
- Apply liberally 15 minutes before sun exposure and as needed.
- Reapply every 2 hours or after swimming, towel drying, perspiring heavily, washing, or in the case of products applied to the lips, after eating or drinking.
- Use water resistant sunscreen if swimming or sweating.
- Sun Protection Measures. Spending time in the sun increases your risk of skin cancer and early skin aging. To decrease this risk, regularly use a sunscreen with a broad spectrum SPF of 15 or higher and other sun protection measures including: limit time in the sun, especially from 10am-2pm, wear long sleeve shirts, pants and sunglasses.
- Children under 6 months: ask a doctor.

Non Medicinal Ingredients

Aloe Barbadensis Leaf Juice [Certified Organic/Organic] , Purified Water (Aqua), Caprylic/Capric Triglycerides, Vegetable Glycerin, Simmondsia Chinensis (Jojoba) Seed Oil, Polyglyceryl-2 Oleate, Polyhydroxystearic Acid, Polyglyceryl-2 Stearate, Helianthus Annuus (Sunflower) Seed Oil, Punica Granatum (Pomegranate) Seed Oil, Hydrogenated Castor Oil, Dimethicone, Magnesium Sulfate, Sorbitan Sesquioleate, Fruit Stem Cells (Argan, Malus Domestica, Solar Vitis) and BioActive Berry Complex, Sodium Hyaluronate, Salix Alba (Willow Bark) Extract, Serenoa Rapens (Saw Palmetto) Fruit Extract, Magnesium Ascorbyl Phosphate (Vitamin C), Borago Officinalis (Borage) Seed Oil, Cucumis Sativus (Cucumber) Fruit Extract, Zea Mays (Corn) Starch, Camellia Sinensis (White Tea) Leaf Extract [Fair Trade/Biologique] , Hibiscus Sabdariffa Flower Extract, Tocopherol, Phenethyl Alcohol, Ethylhexylglycerin, Citrus Aurantium Dulcis (Orange) Peel Oil, Cymbopogon Martini (Palmarosa) Leaf Oil

Other Information

- Protect the product in this container from excessive heat and direct sun.

Questions

Call (888) 898-6955 or visit www.Andalou.com

Dist. by Andalou Naturals
Novato, CA 94945 USA

PRINCIPAL DISPLAY PANEL - 58 mL Tube Carton

IMPROVED!

ANDALOU
NATURALS

NON
GMO

BB

Argan Stem Cell
BENEFIT BALM

Un-Tinted
SPF 30

with Argan Stem Cells
Energized Renewal

Broad Spectrum Protection

FRUIT
STEM
CELL

SCIENCE®

CLEAR SKIN

NPN 80042784

2 fl oz e 58 mL